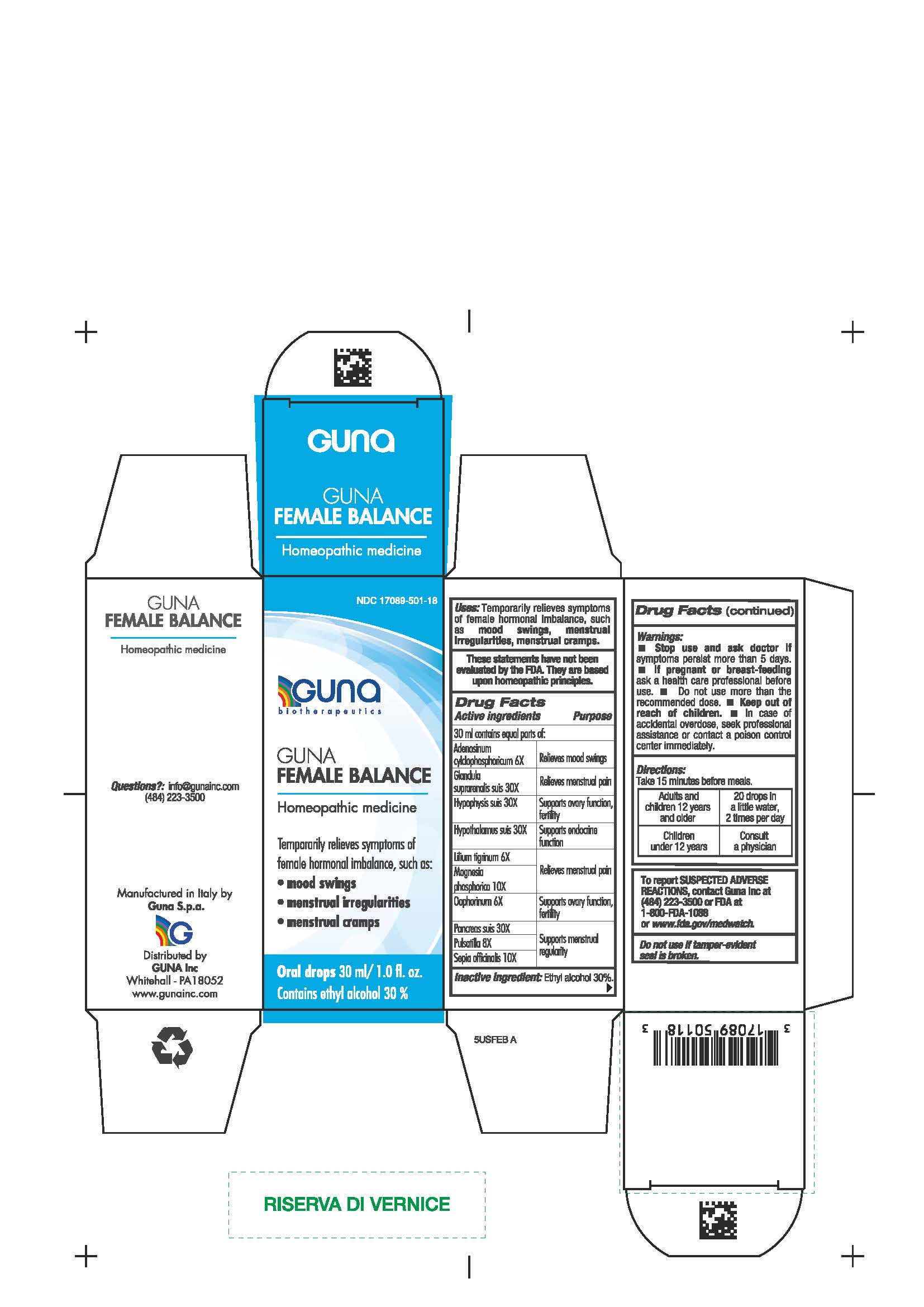 DRUG LABEL: GUNA FEMALE SUPPORT
NDC: 17089-501 | Form: SOLUTION/ DROPS
Manufacturer: Guna spa
Category: homeopathic | Type: HUMAN OTC DRUG LABEL
Date: 20210212

ACTIVE INGREDIENTS: LILIUM LANCIFOLIUM WHOLE FLOWERING 6 [hp_X]/30 mL; SUS SCROFA OVARY 6 [hp_X]/30 mL; SEPIA OFFICINALIS JUICE 10 [hp_X]/30 mL; ADENOSINE CYCLIC PHOSPHATE 6 [hp_X]/30 mL; SUS SCROFA PITUITARY GLAND 30 [hp_X]/30 mL; SUS SCROFA HYPOTHALAMUS 30 [hp_X]/30 mL; SUS SCROFA ADRENAL GLAND 30 [hp_X]/30 mL; SUS SCROFA PANCREAS 30 [hp_X]/30 mL; MAGNESIUM PHOSPHATE, DIBASIC TRIHYDRATE 10 [hp_X]/30 mL; PULSATILLA VULGARIS 8 [hp_X]/30 mL
INACTIVE INGREDIENTS: ALCOHOL 9 mL/30 mL

GUNA FEMALE SUPPORT

DIRECTIONS

Take 15 minutes before meals.

Adults and children 12 years and older: 20 drops in a little water, 2 times per day

Children under 12 years: consult a physician

ACTIVE INGREDIENTS/PURPOSE

Adenosinum cylclophosphoricum 6X Relieves mood swings

Glandula suprarenalis suis 30X Relieves menstrual pain

Hypophysis suis 30X Supports ovary function, fertility

Hypothalamus suis 30X Supports endocrine function

Lilium tigrinum 6X Relieves menstrual pain

Magnesia phosphorica 10X Relieves menstrual pain

Oophorinum 6X Supports ovary function, fertility

Pancreas suis 30X Supports menstrual regularity

Pulsatilla 8X Supports menstrual regularity

Sepia officinalis 10X Supports menstrual regularity

USES

Temporarily relieves symptoms of female hormonal imbalance, such as:

- mood swings
- menstrual irregularities
- menstrual cramps.

Inactive ingredient: Ethyl alcohol 30%.

QUESTIONS

info@gunainc.com
Tel. (484) 223-3500

WARNINGS

Keep out of reach of children.

INDICATIONS AND USAGE

Take 15 minutes before meals.

PREGNANCY

If pregnant or breast-feeding ask a health care profesisonal before use.

WARNINGS

- Stop use and ask doctor if symptoms worsen or persist more than 5 days.
- If pregnant or breast-feeding ask a health care professional before use.
- Keep out of reach of children.
- In case of accidental overdose, seek professional assistance or contact a poison control center immediately
- Contains ethyl alcohol 30%